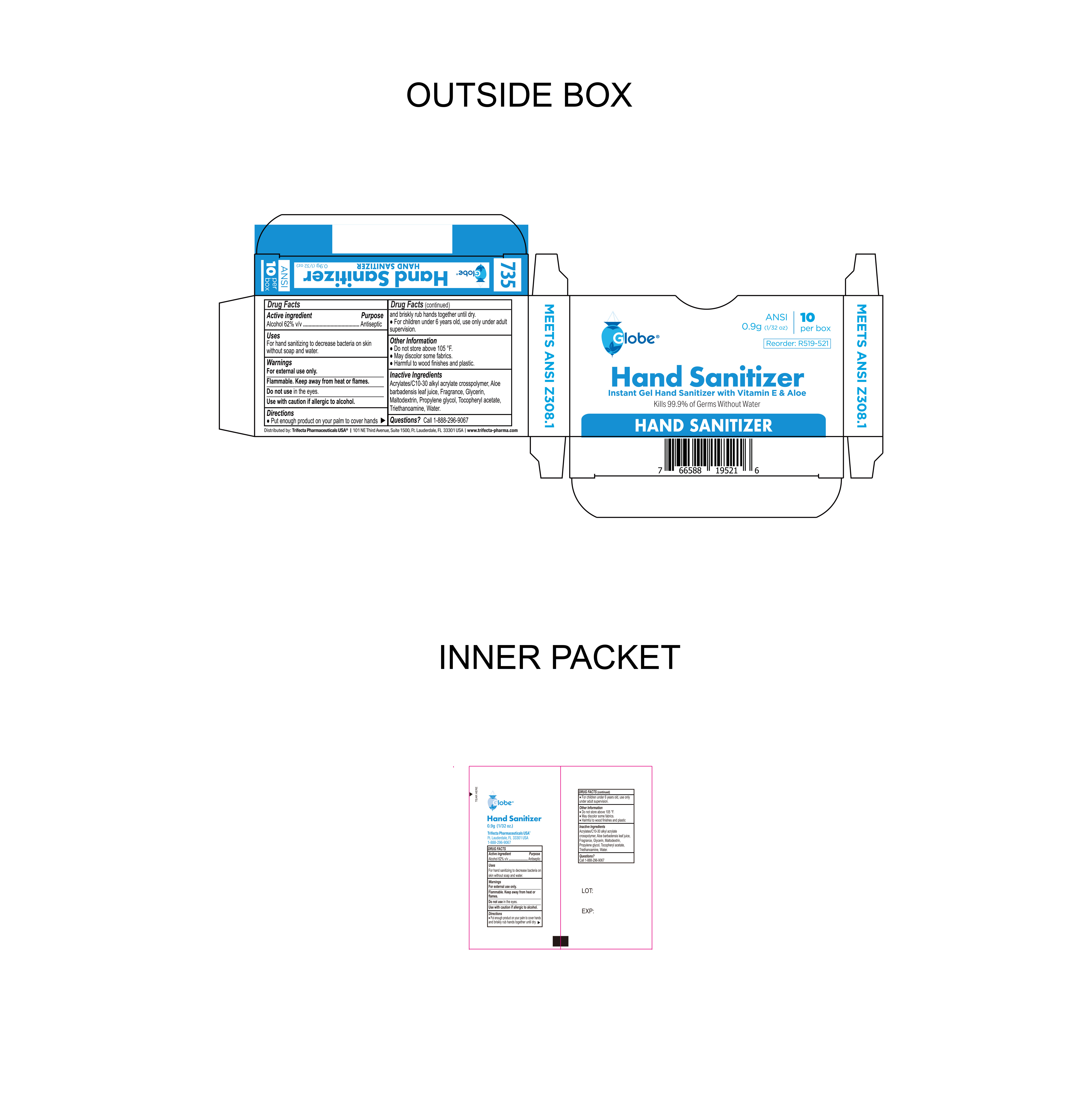 DRUG LABEL: Hand Sanitizer
NDC: 69396-137 | Form: GEL
Manufacturer: Trifecta Pharmaceuticals USA
Category: otc | Type: HUMAN OTC DRUG LABEL
Date: 20241231

ACTIVE INGREDIENTS: ALCOHOL 62 g/100 g
INACTIVE INGREDIENTS: .ALPHA.-TOCOPHEROL ACETATE; ACRYLATES/C10-30 ALKYL ACRYLATE CROSSPOLYMER (60000 MPA.S); TROLAMINE; FRAGRANCE 13576; PROPYLENE GLYCOL; MALTODEXTRIN; GLYCERIN; ALOE VERA LEAF; WATER

Globe Hand Sanitizer

Active Ingredient

Alcohol 62% v/v

Purpose

Antiseptic

Uses

For hand sanitizing to decrease bacteria on skin without soap and water

Warnings

- for external use only
- Use with caution if allergic to alcohol.
- Flammable. Keep away from heat or flames.

Do not use

- in the eyes

Directions

Put enough product on your palm to cover hands and briskly rub hands together until dry.

Keep out of reach of Children

For Children under 6 years old, use only under adult supervision

Inactive Ingredients

Aloe barbadensis leaf juice, Acrylates/C10-30 alkyl acrylate crosspolymer, Fragrance, Glycerin, Maltodextrin, Propylene glycol, Tocopheryl acetate, Triethanoamine, water.

Other Information

- Do not store above 105°F
- May discolor some fabrics
- Harmful to wood finishes and plastic

Other Information

Distributed By:

Trifecta Pharmaceuticals USA®

101 NE Third Avenue, Suite 1500

Ft. Lauderdale, FL. 33301 USA

www.trifecta-pharma.com

1-888-296-9067